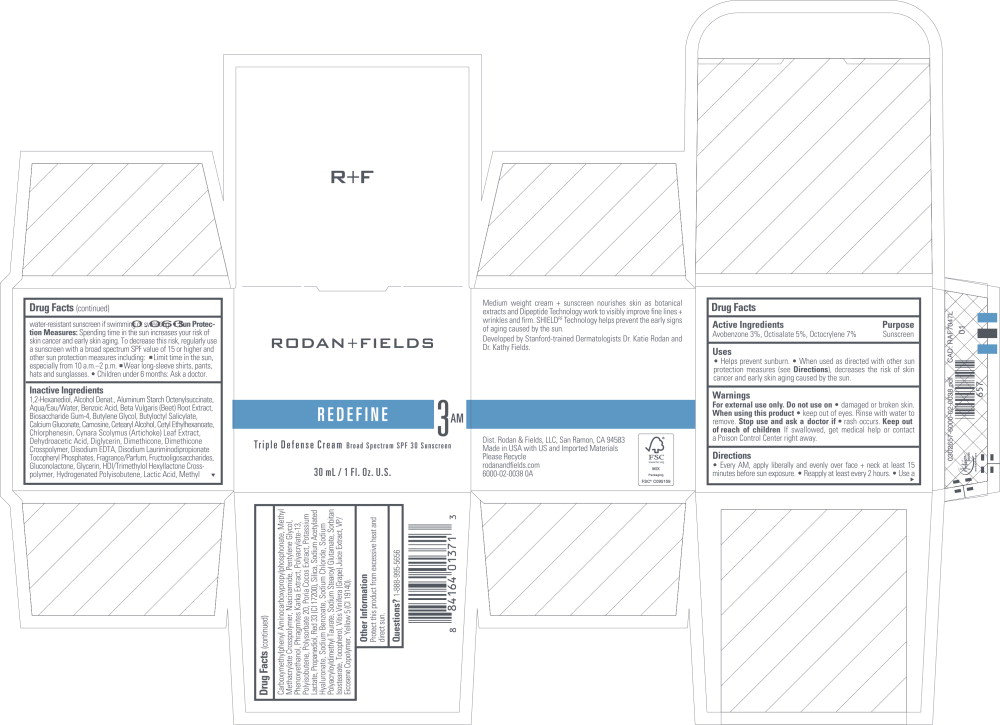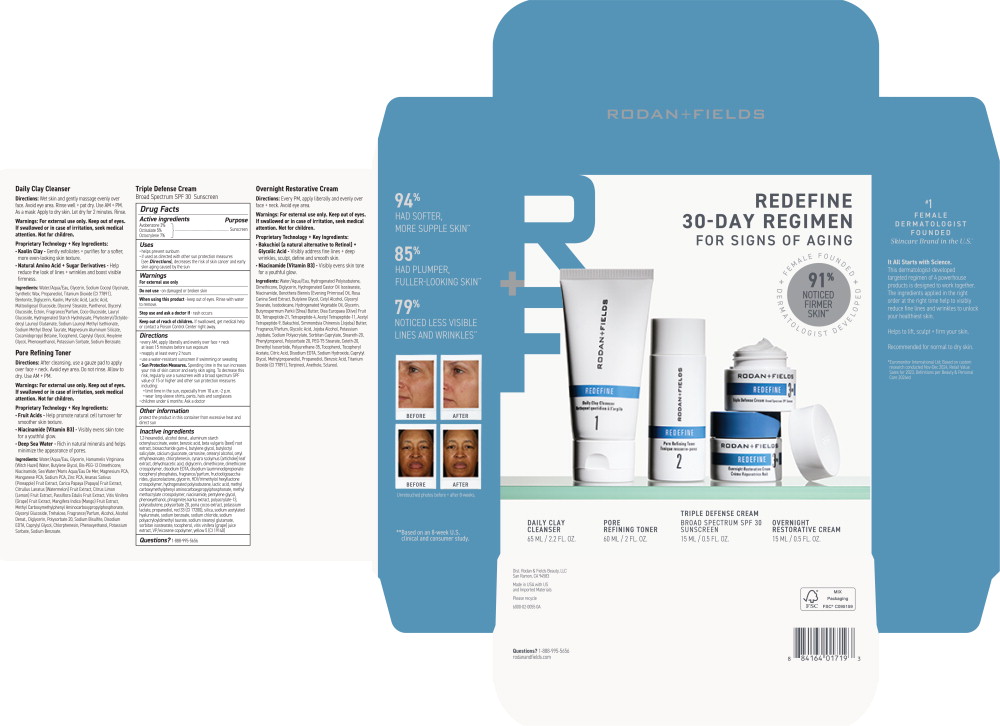 DRUG LABEL: REDEFINE Triple Defense
NDC: 14222-2251 | Form: CREAM
Manufacturer: Rodan & Fields
Category: otc | Type: HUMAN OTC DRUG LABEL
Date: 20260127

ACTIVE INGREDIENTS: OCTOCRYLENE 0.07 g/1 mL; OCTISALATE 0.05 g/1 mL; AVOBENZONE 0.03 g/1 mL
INACTIVE INGREDIENTS: 1,2-HEXANEDIOL; ALCOHOL; ALUMINUM STARCH OCTENYLSUCCINATE; WATER; BENZOIC ACID; BETA VULGARIS; BIOSACCHARIDE GUM-4; BUTYLENE GLYCOL; BUTYLOCTYL SALICYLATE; CALCIUM GLUCONATE; CARNOSINE; CETOSTEARYL ALCOHOL; CETYL ETHYLHEXANOATE; CHLORPHENESIN; CYNARA SCOLYMUS LEAF; DEHYDROACETIC ACID; DIGLYCERIN; DIMETHICONE; DIMETHICONE CROSSPOLYMER (450000 MPA.S); EDETATE DISODIUM ANHYDROUS; DISODIUM LAURIMINODIPROPIONATE TOCOPHERYL PHOSPHATES; BETA VULGARIS ROOT FRUCTOOLIGOSACCHARIDES; GLUCONOLACTONE; GLYCERIN; HEXAMETHYLENE DIISOCYANATE/TRIMETHYLOL HEXYLLACTONE CROSSPOLYMER; HYDROGENATED POLYBUTENE (1300 MW); LACTIC ACID, UNSPECIFIED FORM; METHYL CARBOXYMETHYLPHENYL AMINOCARBOXYPROPYLPHOSPHONATE; METHYL METHACRYLATE/GLYCOL DIMETHACRYLATE CROSSPOLYMER; NIACINAMIDE; PENTYLENE GLYCOL; PHENOXYETHANOL; PHRAGMITES KARKA WHOLE; POLYACRYLATE-13; POLYISOBUTYLENE (2300 MW); POLYSORBATE 20; FU LING; POTASSIUM LACTATE; PROPANEDIOL; D&C RED NO. 33; SILICON DIOXIDE; SODIUM ACETYLATED HYALURONATE; SODIUM BENZOATE; SODIUM CHLORIDE; SODIUM POLYACRYLOYLDIMETHYL TAURATE; SODIUM STEAROYL GLUTAMATE; SORBITAN ISOSTEARATE; TOCOPHEROL; WINE GRAPE JUICE; EICOSYL POVIDONE; FD&C YELLOW NO. 5

Drug Facts

Active ingredients

Avobenzone 3%

Octisalate 5%

Octocrylene 7%

Purpose

Sunscreen

Sunscreen

Sunscreen

Uses

- helps prevent sunburn
- if used as directed with other sun protection measures

(see Directions), decreases the risk of skin cancer and early skin aging caused by the sun

Warnings

For external use only

Do not use

- on damaged or broken skin

When using this product

- keep out of eyes. Rinse with water to remove.

Stop use and ask a doctor if

- rash occurs

Keep out of reach of children. If swallowed, get medical help or contact a Poison Control Center right away.

Directions

- every AM, apply liberally and evenly over face + neck at least 15 minutes before sun exposure
- reapply at least every 2 hours
- use a water-resistant sunscreen if swimming or sweating
- Sun Protection Measures. Spending time in the sun increases your risk of skin cancer and early skin aging. To decrease this risk, regularly use a sunscreen with a broad spectrum SPF value of 15 or higher and other sun protection measures including:
  - limit time in the sun, especially from 10 a.m.-2 p.m.
  - wear long-sleeve shirts, pants, hats and sunglasses
- children under 6 months: Ask a doctor

Other information

protect the product in this container from excessive heat and direct sun

Inactive ingredients

1,2-hexanediol, alcohol denat., aluminum starch octenylsuccinate, water, benzoic acid, beta vulgaris (beet) root extract, biosaccharide gum-4, butylene glycol, butyloctyl salicylate, calcium gluconate, carnosine, cetearyl alcohol, cetyl ethylhexanoate, chlorphenesin, cynara scolymus (artichoke) leaf extract, dehydroacetic acid, diglycerin, dimethicone, dimethicone crosspolymer, disodium EDTA, disodium lauriminodipropionate tocopheryl phosphates, fragrance/parfum, fructooligosaccharides, gluconolactone, glycerin, HDI/trimethylol hexyllactone crosspolymer, hydrogenated polyisobutene, lactic acid, methyl carboxymethylphenyl aminocarboxypropylphosphonate, methyl methacrylate crosspolymer, niacinamide, pentylene glycol, phenoxyethanol, phragmites karka extract, polyacrylate-13, polyisobutene, polysorbate 20, poria cocos extract, potassium lactate, propanediol, red 33 (Cl 17200), silica, sodium acetylated hyaluronate, sodium benzoate, sodium chloride, sodium polyacryloyldimethyl taurate, sodium stearoyl glutamate, sorbitan isostearate, tocopherol, vitis vinifera (grape) juice extract, VP/eicosene copolymer, yellow 5 (Cl 19140)

Questions?

1-888-995-5656

Principal Display Panel - 15 mL Carton Label

RODAN+FIELDS

REDEFINE
30-DAY REGIMEN
FOR SIGNS OF AGING

FEMALE FOUNDED + DERMATOLOGIST DEVELOPED

91%
NOTICED
FIRMER
SKIN**

DAILY CLAY
CLEANSER
65 ML/2.2 FL. OZ.

PORE
REFINING TONER
60 ML/2 FL. OZ.

TRIPLE DEFENSE CREAM
BROAD SPECTRUM SPF 30
SUNSCREEN

15 ML/0.5 FL. OZ.

OVERNIGHT
RESTORATIVE CREAM

15 ML/0.5 FL. OZ.

Principal Display Panel - 15 mL Jar Label

RODAN+FIELDS

REDEFINE 3 AM

Triple Defense Cream Broad Spectrum SPF 30 Sunscreen